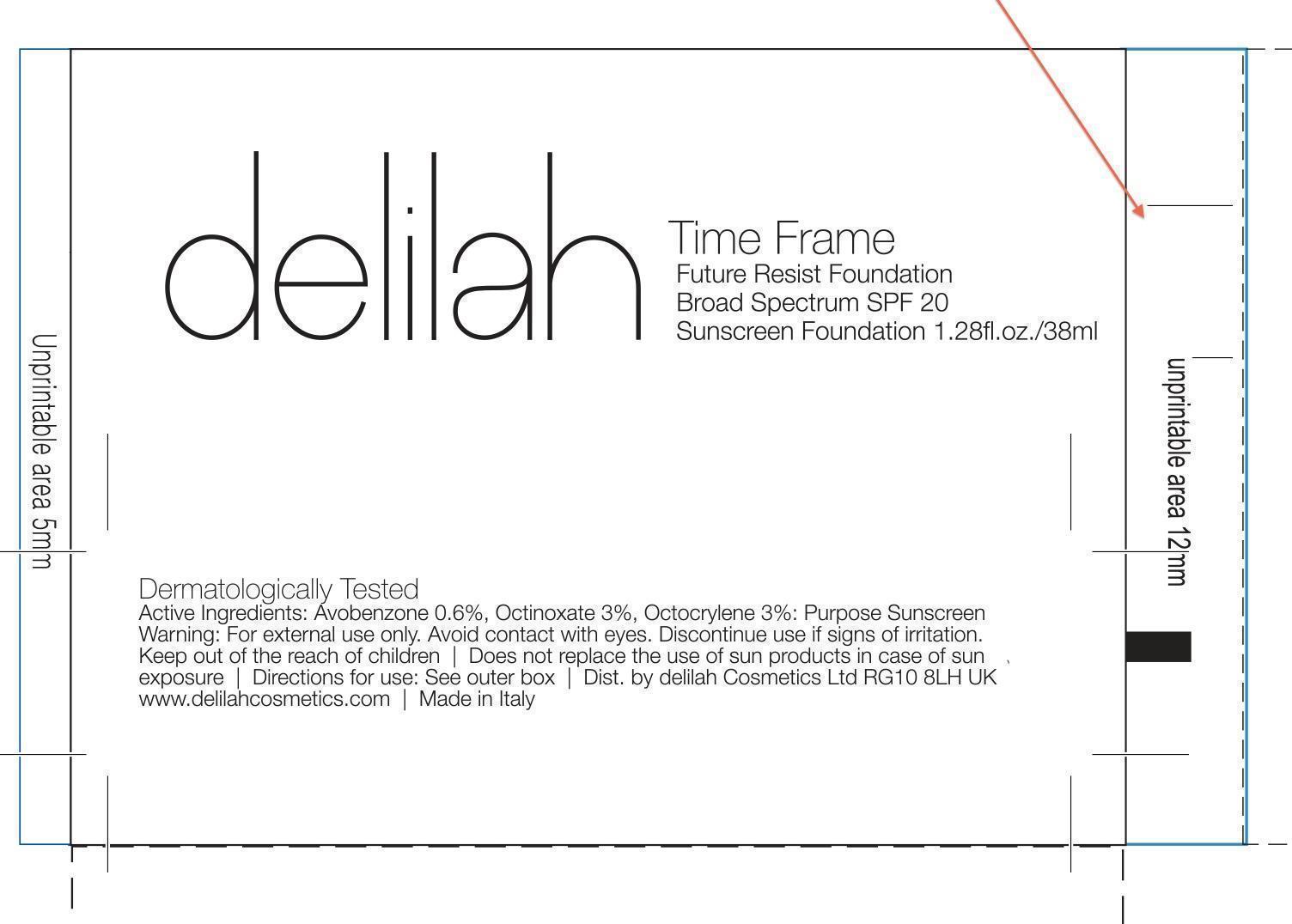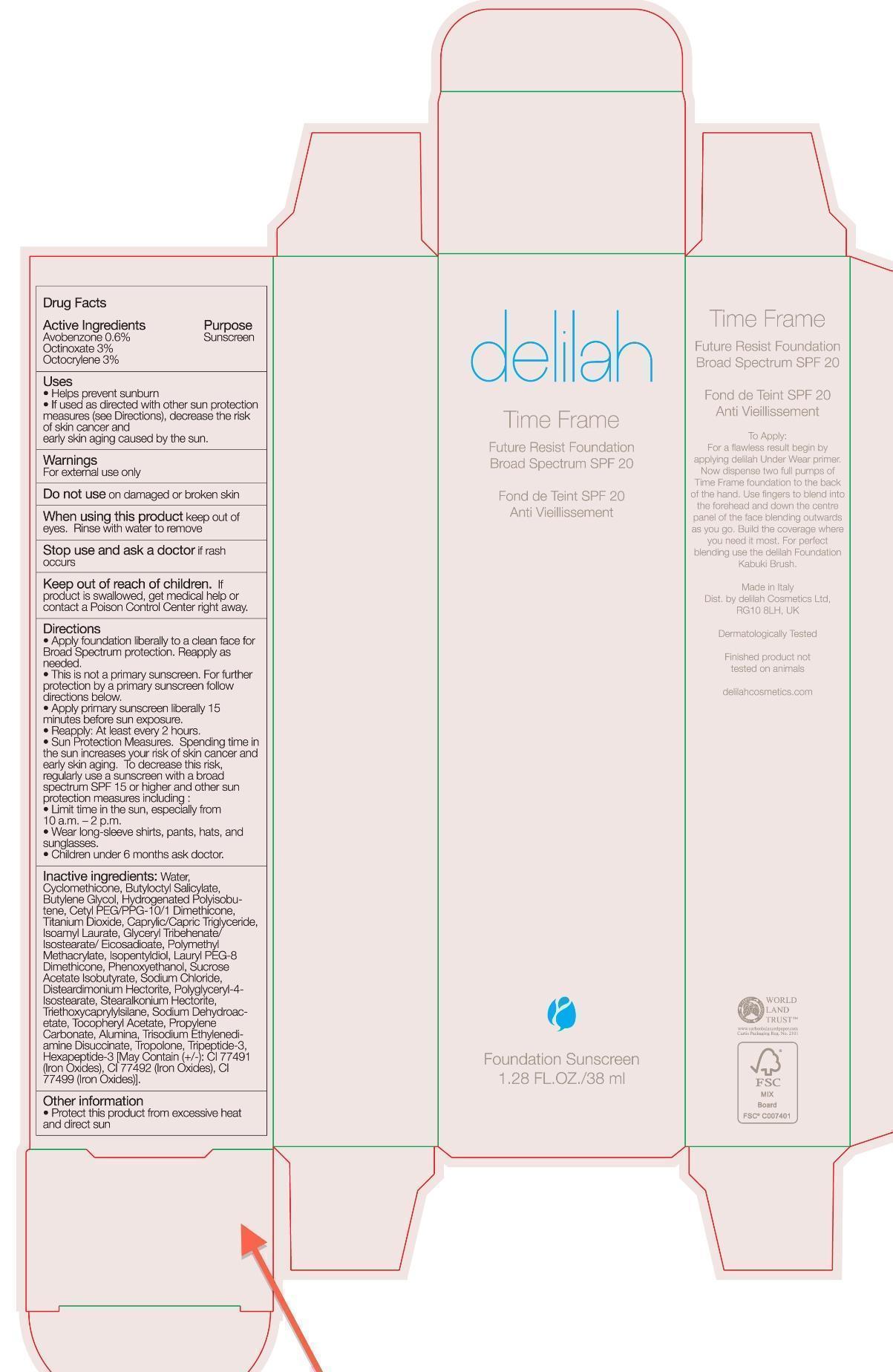 DRUG LABEL: Time Frame Future Resist Foundation Broad Spectrum SPF 20 Truffle
NDC: 69000-011 | Form: SOLUTION
Manufacturer: Delilah Cosmetics
Category: otc | Type: HUMAN OTC DRUG LABEL
Date: 20150427

ACTIVE INGREDIENTS: AVOBENZONE 0.6 g/100 mL; OCTINOXATE 3 g/100 mL; OCTOCRYLENE 3 g/100 mL
INACTIVE INGREDIENTS: WATER; CYCLOMETHICONE; BUTYLOCTYL SALICYLATE; BUTYLENE GLYCOL; HYDROGENATED POLYBUTENE (1300 MW); CETYL PEG/PPG-10/1 DIMETHICONE (HLB 2); MEDIUM-CHAIN TRIGLYCERIDES; ISOAMYL LAURATE; GLYCERYL TRIBEHENATE/ISOSTEARATE/EICOSANDIOATE; POLY(METHYL METHACRYLATE; 450000 MW); ISOPENTYLDIOL; PHENOXYETHANOL; SUCROSE ACETATE ISOBUTYRATE; SODIUM CHLORIDE; DISTEARDIMONIUM HECTORITE; POLYGLYCERYL-4 ISOSTEARATE; STEARALKONIUM HECTORITE; TRIETHOXYCAPRYLYLSILANE; SODIUM DEHYDROACETATE; .ALPHA.-TOCOPHEROL ACETATE; PROPYLENE CARBONATE; ALUMINUM OXIDE; TROPOLONE; FERRIC OXIDE RED; FERRIC OXIDE YELLOW; FERROSOFERRIC OXIDE

Future resist Foundation Broad Spectrum SPF 20 Truffle

Active Ingredients Purpose

Avobenzone 0.6% Sunscreen

Octinoxate 3% Sunscreen

Octocrylene 3% Sunscreen

Uses

Helps prevent Sunburn

If used as directed with other sun protection measures (see Directions), decrease the risk of skin cancer and early skin aging caused by the sun.

Keep out of reach of children. If product is swallowed, get medical help contact a Poison Control Center right away.

Stop use and ask a dcotor if rash occurs.

Warnings

For external use only

Do not use on damaged or broken skin

When using this product keep out of eyes. Rinse with water to remove.

Directions

Apply foundation liberally to clean face for Broad Spectrum protection. Reapply as needed.

This is not a primary Sunscreen. For further protection by a primary Sunscreen follow directions below.

Apply primary Sunscreen liberally 15 minutes before sun exposure

Reapply at least every 2 hours.

Sun Protection measures. Spending time in the sun increases your risk of skin cancer and early skin aging. To decrease this risk, regularly use a sunscreen with a broad spectrum SPF 15 or higher and other sun protection measures including:

Limit time in the sun, especially 10 a.m. - 2 p.m.

Wear long-sleeve shirts, pants, hats, and sunglasses

Children under 6 months ask doctor

INACTIVE INGREDIENT

Caprylic/Capric TriglycerideInactive Ingredients: Water/Aqua, Cyclomethicone, Butyloctyl Salicylate, Butylene Glycol, Hydrogenated Polyisobutene, Cetyl PEG/PPG-10/1 Dimethicone, Titanium Dioxide, Caprylic/Capric Triglyceride, Isoamyl Laurate, Glyceryl Tribehenate/Isostearate/Eicosadioate, Polymethyl Methacrylate, Isopentyldiol, Lauryl PEG-8 Dimethicone, Phenoxyethanol, Sucrose Acetate Isobutyrate Sodium Chloride, Disteardimonium Hectorite, Polyglyceryl-4-Isostearate, Stearalkonium Hectorite, Triethoxycaprylylsilane, Sodium Dehydroacetate, Tocopheryl Acetate, Propylene Carbonate, Alumina, Trisodium Ethylenediamine Dissucinate, Tropolone, Tripeptide-3, Hexapeptide-3 [May Contain (+/-): CI 77491 (Iron Oxides), CI 77492 (Iron Oxide), CI 77499 (Iron Oxides)].

PACKAGE LABEL

delilah

Time Frame

Future Resist Foundation Broad Spectrum SPF 20 Truffle

Fond de Teint SPF 20

Anti Vieillissement

Foundation Sunscreen

1.28 Fl Oz/ 38 ml